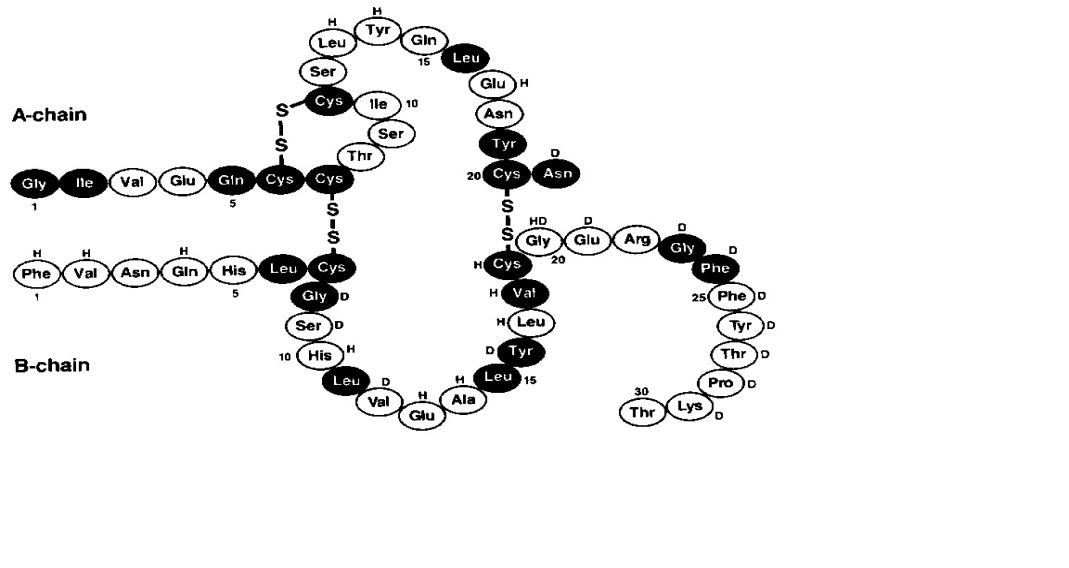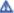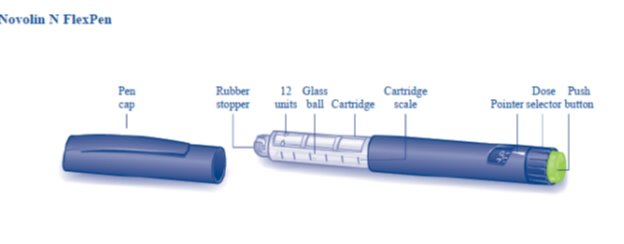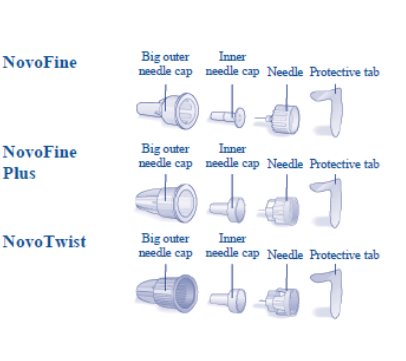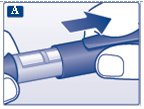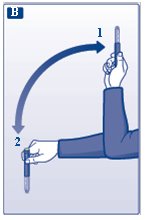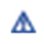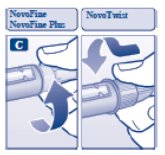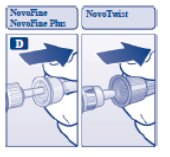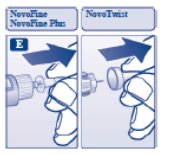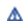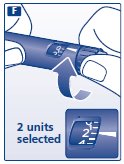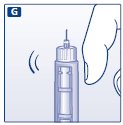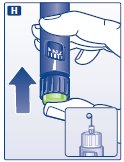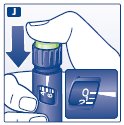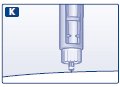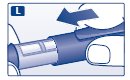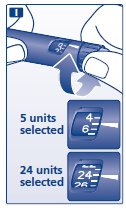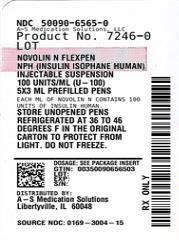 DRUG LABEL: Novolin
NDC: 50090-6565 | Form: INJECTION, SUSPENSION
Manufacturer: A-S Medication Solutions
Category: otc | Type: HUMAN OTC DRUG LABEL
Date: 20230721

ACTIVE INGREDIENTS: INSULIN HUMAN 100 [iU]/1 mL
INACTIVE INGREDIENTS: SODIUM PHOSPHATE, DIBASIC, UNSPECIFIED FORM; GLYCERIN; METACRESOL; PHENOL; PROTAMINE SULFATE; ZINC; WATER; HYDROCHLORIC ACID; SODIUM HYDROXIDE

HIGHLIGHTS OF PRESCRIBING INFORMATION

These highlights do not include all the information needed to use NOVOLIN N safely and effectively. See full prescribing information for NOVOLIN N.
NOVOLIN® N (insulin isophane human) injectable suspension, for subcutaneous use
Initial U.S. Approval: 1991

1 INDICATIONS AND USAGE

NOVOLIN N is an intermediate-acting human insulin indicated to improve glycemic control in adults and pediatric patients with diabetes mellitus. (1)

2 DOSAGE AND ADMINISTRATION

- See Full Prescribing Information for important administration instructions. (2.1)
- Inject subcutaneously in abdominal wall, thigh, upper arm, or buttocks and rotate injection sites to reduce the risk of lipodystrophy and localized cutaneous amyloidosis. (2.1)
- Individualize and adjust dosage based on metabolic needs, blood glucose monitoring results and glycemic control goal. (2.2)
- Administer NOVOLIN N once or twice daily. (2.2)
- In patients with type 1 diabetes, NOVOLIN N should generally be used in regimens that include a short-acting insulin. (2.2)
- NOVOLIN N can be mixed with NOVOLIN R. (2.4)

3 DOSAGE FORMS AND STRENGTHS

Injectable suspension: 100 units/mL (U-100) is available as:

- 10 mL multiple-dose vial (3)
- 3 mL single-patient-use NOVOLIN N FlexPen prefilled pen (3)

4 CONTRAINDICATIONS

- During episodes of hypoglycemia (4)
- Hypersensitivity to NOVOLIN N or any of its excipients (4)

5 WARNINGS AND PRECAUTIONS

- Never share a NOVOLIN N FlexPen or syringe between patients, even if the needle is changed. (5.1)
- Hyperglycemia or Hypoglycemia with Changes in Insulin Regimen: Make changes to a patient’s insulin regimen (e.g., insulin strength, manufacturer, type, injection site or method of administration) under close medical supervision with increased frequency of blood glucose monitoring. (5.2)
- Hypoglycemia: May be life-threatening. Increase frequency of blood glucose monitoring with changes to: insulin dosage, co-administered glucose lowering medications, meal pattern, physical activity; in patients with renal or hepatic impairment; and in patients with hypoglycemia unawareness. (5.3)
- Hypoglycemia Due to Medication Errors: Accidental mix-ups between insulin products can occur. Instruct patients to check insulin labels before injection. (5.4)
- Hypersensitivity Reactions: Severe, life-threatening, generalized allergy, including anaphylaxis, can occur. Discontinue NOVOLIN N, monitor, and treat if indicated. (5.5)
- Hypokalemia: May be life-threatening. Monitor potassium levels in patients at risk for hypokalemia and treat if indicated. (5.6)
- Fluid Retention and Heart Failure with Concomitant Use of Thiazolidinediones (TZDs): Observe for signs and symptoms of heart failure; consider dosage reduction or discontinuation if heart failure occurs. (5.7)

6 ADVERSE REACTIONS

Adverse reactions observed with NOVOLIN N include hypoglycemia, allergic reactions, injection site reactions, lipodystrophy, weight gain and edema. (6)

To report SUSPECTED ADVERSE REACTIONS, contact Novo Nordisk Inc. at 1-800-727-6500 or FDA at 1-800-FDA-1088 or www.fda.gov/medwatch.

7 DRUG INTERACTIONS

- Drugs that Affect Glucose Metabolism: Adjustment of insulin dosage may be needed. (7)
- Antiadrenergic Drugs (e.g., beta-blockers, clonidine, guanethidine, and reserpine): Signs and symptoms of hypoglycemia may be reduced or absent. (5.3, 7)

FULL PRESCRIBING INFORMATION

1 INDICATIONS AND USAGE

NOVOLIN N is indicated to improve glycemic control in adults and pediatric patients with diabetes mellitus.

2 DOSAGE AND ADMINISTRATION

2.1 Important Administration Instructions

- Always check insulin labels before administration [see Warnings and Precautions (5.4)].
- NOVOLIN N is a suspension that must be resuspended immediately before use. Resuspension is easier when the insulin has reached room temperature.
- To resuspend vial, roll the vial gently in your hands in a horizontal position 10 times until the suspension appears uniformly white and cloudy. Inject immediately.
- To resuspend FlexPen, gently move the pen up and down 20 times so the glass ball moves from one end of the cartridge to the other until the suspension appears uniformly white and cloudy. Inject immediately.
- Inspect NOVOLIN N visually before use. Do not use NOVOLIN N if discoloration or particulate matter is seen.
- Administer NOVOLIN N by subcutaneous injection in the abdominal wall, thigh, upper arm, or buttocks.
- Rotate the injection site within the same region from one injection to the next to reduce the risk of lipodystrophy and localized cutaneous amyloidosis. Do not inject into areas of lipodystrophy or localized cutaneous amyloidosis [see Warnings and Precautions (5.2), Adverse Reactions (6)].
- During changes to a patient’s insulin regimen, increase the frequency of blood glucose monitoring [see Warnings and Precautions (5.2)].
- Do not administer NOVOLIN N intravenously and do not use in an insulin infusion pump.

2.2 Dosage Information

- Individualize and adjust the dosage of NOVOLIN N based on the individual's metabolic needs, blood glucose monitoring results and glycemic control goal.
- Administer NOVOLIN N once or twice daily.
- In patients with type 1 diabetes, NOVOLIN N should generally be used in regimens that include a short-acting insulin.
- Dosage adjustments may be needed with changes in physical activity, changes in meal patterns (i.e., macronutrient content or timing of food intake), changes in renal or hepatic function or during acute illness [see Warnings and Precautions (5.2, 5.3) and Use in Specific Populations (8.6, 8.7)].
- Dosage adjustment may be needed when switching from another insulin to NOVOLIN N [see Warnings and Precautions (5.2)].

2.3 Dosage Adjustment due to Drug Interactions

- Dosage adjustment may be needed when NOVOLIN N is co-administered with certain drugs [see Drug Interactions (7)].

2.4 Instructions for Mixing with Other Insulins

- NOVOLIN N can be mixed in the same syringe with NOVOLIN R.
- When mixing, the NOVOLIN R should be drawn into the syringe first, followed by the NOVOLIN N. The mixture should be injected immediately after mixing.

3 DOSAGE FORMS AND STRENGTHS

Injectable suspension: 100 units/mL (U-100) white and cloudy suspension available as:
2. 10 mL multiple-dose vial
3. 3 mL single-patient-use NOVOLIN N FlexPen prefilled pen

4 CONTRAINDICATIONS

NOVOLIN N is contraindicated:

- During episodes of hypoglycemia [see Warnings and Precautions (5.3)]
- In patients who have hypersensitivity reactions to NOVOLIN N or any of its excipients [see Warnings and Precautions (5.5)]

5 WARNINGS AND PRECAUTIONS

5.1 Never Share a NOVOLIN N FlexPen or Syringe between Patients

NOVOLIN N FlexPen must never be shared between patients, even if the needle is changed. Patients using NOVOLIN N vials must never share needles or syringes with another person. Sharing poses a risk for transmission of blood-borne pathogens.

5.2 Hyperglycemia or Hypoglycemia with Changes in Insulin Regimen

Changes in an insulin regimen (e.g., insulin strength, manufacturer, type, injection site or method of administration) may affect glycemic control and predispose to hypoglycemia [see Warnings and Precautions (5.3)] or hyperglycemia. Repeated insulin injections into areas of lipodystrophy or localized cutaneous amyloidosis have been reported to result in hyperglycemia; and a sudden change in the injection site (to an unaffected area) has been reported to result in hypoglycemia [see Adverse Reactions (6)].

Make any changes to a patient’s insulin regimen under close medical supervision with increased frequency of blood glucose monitoring. Advise patients who have repeatedly injected into areas of lipodystrophy or localized cutaneous amyloidosis to change the injection site to unaffected areas and closely monitor for hypoglycemia. For patients with type 2 diabetes, dosage adjustments of concomitant anti-diabetic products may be needed.

5.3 Hypoglycemia

Hypoglycemia is the most common adverse reaction of all insulins, including NOVOLIN N. Severe hypoglycemia can cause seizures, may lead to unconsciousness may be life threatening or cause death. Hypoglycemia can impair concentration ability and reaction time; this may place the patient and others at risk in situations where these abilities are important (e.g., driving or operating other machinery).

Hypoglycemia can happen suddenly and symptoms may differ in each patient and change over time in the same patient. Symptomatic awareness of hypoglycemia may be less pronounced in patients with longstanding diabetes in patients with diabetic neuropathy, in patients using medications that block the sympathetic nervous system (e.g., beta-blockers) [see Drug Interactions (7)], or in patients who experience recurrent hypoglycemia.

Risk Factors for Hypoglycemia

The risk of hypoglycemia after an injection is related to the duration of action of the insulin and, in general, is highest when the glucose lowering effect of the insulin is maximal. As with all insulins, the glucose lowering effect time course of NOVOLIN N may vary in different individuals or at different times in the same individual and depends on many conditions, including the area of injection as well as the injection site blood supply and temperature. Other factors which may increase the risk of hypoglycemia include changes in meal pattern (e.g., macronutrient content or timing of meals), changes in level of physical activity, or changes to concomitant drugs [see Drug Interactions (7)]. Patients with renal or hepatic impairment may be at higher risk of hypoglycemia [see Use in Specific Populations (8.6, 8.7)].

Risk Mitigation Strategies for Hypoglycemia

Patients and caregivers must be educated to recognize and manage hypoglycemia. Self-monitoring of blood glucose plays an essential role in the prevention and management of hypoglycemia. In patients at higher risk for hypoglycemia and patients who have reduced symptomatic awareness of hypoglycemia, increased frequency of blood glucose monitoring is recommended.

5.4 Hypoglycemia Due to Medication Errors

Accidental mix-ups between NOVOLIN N and other insulin products have been reported. To avoid medication errors between NOVOLIN N and other insulins, instruct patients to always check the insulin label before each injection.

5.5 Hypersensitivity Reactions

Severe, life-threatening, generalized allergy, including anaphylaxis, can occur with NOVOLIN N. Generalized allergy to insulin may manifest as a whole body rash (including pruritus), dyspnea, wheezing, hypotension, tachycardia, or diaphoresis. If hypersensitivity reactions occur, discontinue NOVOLIN N, treat per standard of care and monitor until symptoms and signs resolve. NOVOLIN N is contraindicated in patients who have had hypersensitivity reactions to isophane insulin human or its excipients.

5.6 Hypokalemia

All insulins, including NOVOLIN N, cause a shift in potassium from the extracellular to intracellular space, possibly leading to hypokalemia. Untreated hypokalemia may cause respiratory paralysis, ventricular arrhythmia, and death. Monitor potassium levels in patients at risk for hypokalemia if indicated (e.g., patients using potassium-lowering medications, patients taking medications sensitive to serum potassium concentration).

5.7 Fluid Retention and Heart Failure with Concomitant Use of PPAR-gamma agonists

Thiazolidinediones (TZDs), which are peroxisome proliferator-activated receptor (PPAR)-gamma agonists, can cause dose-related fluid retention when used in combination with insulin. Fluid retention may lead to or exacerbate heart failure. Patients treated with insulin, including NOVOLIN N, and a PPAR-gamma agonist should be observed for signs and symptoms of heart failure. If heart failure develops, it should be managed according to current standards of care, and discontinuation or dose reduction of the PPAR-gamma agonist must be considered.

6 ADVERSE REACTIONS

The following adverse reactions are also discussed elsewhere in the labeling:

- Hypoglycemia [see Warnings and Precautions (5.3)]
- Hypoglycemia Due to Medication Errors [see Warnings and Precautions (5.4)]
- Hypersensitivity Reactions [see Warnings and Precautions (5.5)]
- Hypokalemia [see Warnings and Precautions (5.6)]
Adverse Reactions from Clinical Studies or Postmarketing Reports
The following additional adverse reactions have been identified during clinical studies or from postmarketing reports with use of NOVOLIN N. Because some of these reactions are reported voluntarily from a population of uncertain size, it is not always possible to reliably estimate their frequency or to establish a causal relationship to drug exposure.
Adverse reactions associated with insulin initiation and glucose control intensification
Intensification or rapid improvement in glucose control has been associated with a transitory, reversible ophthalmologic refraction disorder, worsening of diabetic retinopathy, and acute painful peripheral neuropathy. Over the long-term, improved glycemic control decreases the risk of diabetic retinopathy and neuropathy.
Hypersensitivity reactions
Severe, life-threatening, generalized allergy, including anaphylaxis.
Hypoglycemia
Hypoglycemia is the most commonly observed adverse reaction in NOVOLIN N.
Hypokalemia
NOVOLIN N can cause a shift in potassium from the extracellular to intracellular space, possibly leading to hypokalemia.
Injection site reactions
NOVOLIN N can cause local injection site reactions including redness, swelling, or itching at the site of injection. These reactions usually resolve in a few days to a few weeks, but in some occasions, may require discontinuation. Localized reactions and generalized myalgias have been reported with the use of metacresol, which is an excipient in NOVOLIN N.
Lipodystrophy
Administration of insulin subcutaneously, including NOVOLIN N, has resulted in lipoatrophy (depression in the skin) or lipohypertrophy (enlargement or thickening of tissue) [see Dosage and Administration (2.1)] in some patients.
Localized Cutaneous Amyloidosis
Localized cutaneous amyloidosis at the injection site has occurred. Hyperglycemia has been reported with repeated insulin injections into areas of localized cutaneous amyloidosis; hypoglycemia has been reported with a sudden change to an unaffected injection site.
Medication Errors
Medication errors in which other insulins have been accidentally substituted for NOVOLIN N have been identified during postapproval use.
Peripheral edema
Insulins, including NOVOLIN N, may cause sodium retention and edema, particularly if previously poor metabolic control is improved by intensified insulin therapy.
Weight gain
Weight gain can occur with insulins including NOVOLIN N, and has been attributed to the anabolic effects of insulin and the decrease in glucosuria.
Immunogenicity
As with all therapeutic proteins, insulin administration may cause anti-insulin antibodies to form. The incidence of antibody formation with NOVOLIN N is unknown.

7 DRUG INTERACTIONS

Table 1: Clinically Significant Drug Interactions with NOVOLIN N

Drugs that May Increase the Risk of Hypoglycemia
Drugs: | Antidiabetic agents, ACE inhibitors, angiotensin II receptor blocking agents, disopyramide, fibrates, fluoxetine, monoamine oxidase inhibitors, pentoxifylline, pramlintide, salicylates, somatostatin analog (e.g., octreotide), and sulfonamide antibiotics
Intervention: | Dose adjustment and increased frequency of glucose monitoring may be required when NOVOLIN N is co-administered with these drugs.
Drugs that May Decrease the Blood Glucose Lowering Effect of NOVOLIN N
Drugs: | Atypical antipsychotics (e.g., olanzapine and clozapine), corticosteroids, danazol, diuretics, estrogens, glucagon, isoniazid, niacin, oral contraceptives, phenothiazines, progestogens (e.g., in oral contraceptives), protease inhibitors, somatropin, sympathomimetic agents (e.g., albuterol, epinephrine, terbutaline), and thyroid hormones.
Intervention: | Dose adjustment and increased frequency of glucose monitoring may be required when NOVOLIN N is co-administered with these drugs.
Drugs that May Increase or Decrease the Blood Glucose Lowering Effect of NOVOLIN N
Drugs: | Alcohol, beta-blockers, clonidine, and lithium salts. Pentamidine may cause hypoglycemia, which may sometimes be followed by hyperglycemia.
Intervention: | Dose adjustment and increased frequency of glucose monitoring may be required when NOVOLIN N is co-administered with these drugs.
Drugs that May Blunt Signs and Symptoms of Hypoglycemia
Drugs: | Beta-blockers, clonidine, guanethidine, and reserpine
Intervention: | Increased frequency of glucose monitoring may be required when NOVOLIN N is co-administered with these drugs.

8 USE IN SPECIFIC POPULATIONS

8.1 Pregnancy

Risk Summary

Available data from published studies over decades have not established an association with human insulin use during pregnancy and major birth defects, miscarriage or adverse maternal or fetal outcomes (see Data). There are risks to the mother and fetus associated with poorly controlled diabetes in pregnancy (see Clinical Considerations). Animal reproduction studies were not performed.

The estimated background risk of major birth defects is 6-10% in women with pre-gestational diabetes with a HbA1c >7 and has been reported to be as high as 20-25% in women with a HbA1c >10. The estimated background risk of miscarriage for the indicated population is unknown. In the U.S. general population, the estimated background risk of major birth defects and miscarriage in clinically recognized pregnancies is 2-4% and 15-20%, respectively.

Clinical Considerations

Disease-associated maternal and/or embryo/fetal risk

Poorly controlled diabetes in pregnancy increases the maternal risk for diabetic ketoacidosis, pre-eclampsia, spontaneous abortions, preterm delivery, and delivery complications. Poorly controlled diabetes increases the fetal risk for major birth defects, stillbirth, and macrosomia-related morbidity.

Data

Human Data

While available studies cannot definitively establish the absence of risk, published data from retrospective studies, open-label, randomized, parallel studies and meta-analyses have not established an association with human insulin use during pregnancy and major birth defects, miscarriage, or adverse maternal or fetal outcomes. All available studies have methodological limitations including lack of blinding, unclear methods of randomization, and small sample size.

8.2 Lactation

Risk Summary

Available data from published literature suggests that exogenous human insulin products, including NOVOLIN N, are transferred into human milk. There are no adverse reactions reported in the breastfed infants in the literature. There are no data on the effects of exogenous human insulin products, including NOVOLIN N, on milk production. The developmental and health benefits of breastfeeding should be considered along with the mother’s clinical need for NOVOLIN N and any potential adverse effects on the breastfed infant from NOVOLIN N or from the underlying maternal condition.

8.4 Pediatric Use

NOVOLIN N is indicated to improve glycemic control in pediatric patients with diabetes mellitus.

The dosage of NOVOLIN N must be individualized in pediatric patients based on metabolic needs and frequent monitoring of blood glucose to reduce the risk of hypoglycemia [see Dosage and Administration (2.2) and Warnings and Precautions (5.2, 5.3)].

8.5 Geriatric Use

The effect of age on the pharmacokinetics and pharmacodynamics of NOVOLIN N has not been studied. Elderly patients using insulin, including NOVOLIN N, may be at increased risk of hypoglycemia due to co-morbid disease [see Warnings and Precautions (5.3)].

8.6 Renal Impairment

The effect of renal impairment on the pharmacokinetics and pharmacodynamics of NOVOLIN N has not been studied. Patients with renal impairment are at increased risk of hypoglycemia and may require more frequent NOVOLIN N dose adjustment and more frequent blood glucose monitoring [see Warnings and Precautions (5.3)].

8.7 Hepatic Impairment

The effect of hepatic impairment on the pharmacokinetics and pharmacodynamics of NOVOLIN N has not been studied. Patients with hepatic impairment are at increased risk of hypoglycemia and may require more frequent NOVOLIN N dose adjustment and more frequent blood glucose monitoring [see Warnings and Precautions (5.3)].

10 OVERDOSAGE

Excess insulin administration may cause hypoglycemia and hypokalemia. Mild episodes of hypoglycemia usually can be treated with oral glucose. Adjustments in drug dosage, meal patterns, or exercise may be needed. More severe episodes with coma, seizure, or neurologic impairment can be treated with intramuscular or subcutaneous glucagon or intravenous glucose. Sustained carbohydrate intake and observation may be necessary because hypoglycemia may recur after apparent clinical recovery. Hypokalemia must be corrected appropriately [see Warnings and Precautions (5.3, 5.6)].

11 DESCRIPTION

Insulin isophane human is produced by recombinant DNA technology, utilizing Saccharomyces cerevisiae (baker’s yeast) as the production organism. Insulin isophane human is a suspension of crystals produced from combining human insulin and protamine sulfate under appropriate conditions for crystal formation. The amino acid sequence of insulin isophane human is identical to human insulin and has the empirical formula C257H383N65O77S6 and a molecular weight of 5808 Da.

Figure 1: Structural formula of human insulin

NOVOLIN N (insulin isophane human) injectable suspension is an intermediate acting human insulin. It is a sterile, white and cloudy suspension that contains insulin isophane human suspension (NPH) for subcutaneous use. Each milliliter of Novolin N contains 100 units of insulin human, dibasic sodium phosphate (1.9 mg), glycerin (16 mg), metacresol (1.5 mg), phenol (0.65 mg), protamine sulfate (approximately 0.35 mg), zinc (33.5 mcg for the vial or 33.2 mcg for the FlexPen), and Water for Injection. Hydrochloric acid 2N and sodium hydroxide 2N may be added to adjust the pH. The pH is 7.1 to 7.5.

12 CLINICAL PHARMACOLOGY

12.1 Mechanism of Action

The primary activity of insulin, including NOVOLIN N is the regulation of glucose metabolism. Insulins lower blood glucose by stimulating peripheral glucose uptake, especially by skeletal muscle and fat, and by inhibiting hepatic glucose production. Insulin inhibits lipolysis and proteolysis, and enhances protein synthesis.

12.2 Pharmacodynamics

The time course of insulin action (i.e., glucose lowering) may vary considerably in different individuals or within the same individual. NOVOLIN N is an intermediate-acting insulin with a variable and dose dependent duration of action of up to 24 hours. When injected subcutaneously, the glucose-lowering effect of NOVOLIN N begins approximately 1 to 2 hours post-dose.

12.3 Pharmacokinetics

The pharmacokinetics of NOVOLIN N have been established.

The effects of gender, age, obesity, renal and hepatic impairment on the pharmacokinetics of NOVOLIN N have not been studied.

13 NONCLINICAL TOXICOLOGY

13.1 Carcinogenesis, Mutagenesis, Impairment of Fertility

Carcinogenicity and fertility studies were not performed in animals.

Human insulin is not mutagenic in the following in vitro tests: The chromosomal aberration assay in human lymphocytes, the micronucleus assay in mouse polychromatic erythrocytes, and the mutation frequency assay in Chinese hamster cells.

16 HOW SUPPLIED/STORAGE AND HANDLING

Product: 50090-6565

NDC: 50090-6565-0 3 mL in a SYRINGE, PLASTIC / 5 in a CARTON

17 PATIENT COUNSELING INFORMATION

Advise the patient to read the FDA-approved patient labeling (Patient Information and Instructions for Use).

Never Share a NOVOLIN N FlexPen or Syringe between Patients

Advise patients using NOVOLIN N vials or NOVOLIN N FlexPen not to share needles, syringes, or FlexPen with another person. Sharing poses a risk for transmission of blood-borne pathogens [see Warnings and Precautions (5.1)].

Hyperglycemia or Hypoglycemia

Inform patients that hypoglycemia is the most common adverse reaction with insulin. Instruct patients on self-management procedures including glucose monitoring, proper injection technique, and management of hypoglycemia and hyperglycemia, especially at initiation of NOVOLIN N therapy. Instruct patients on handling of special situations such as intercurrent conditions (illness, stress, or emotional disturbances), an inadequate or skipped insulin dose, inadvertent administration of an increased insulin dose, inadequate food intake, and skipped meals. Instruct patients on the management of hypoglycemia [see Warnings and Precautions (5.3)].

Inform patients that their ability to concentrate and react may be impaired as a result of hypoglycemia. Advise patients who have frequent hypoglycemia or reduced or absent warning signs of hypoglycemia to use caution when driving or operating machinery.

Advise patients that changes in insulin regimen can predispose to hyperglycemia or hypoglycemia and that changes in insulin regimen should be made under close medical supervision [see Warnings and Precautions (5.2)].

Hypoglycemia due to Medication Errors

Instruct patients to always check the insulin label before each injection to avoid mix-ups between insulin products [see Warnings and Precautions (5.4)].

Hypersensitivity Reactions

Advise patients that hypersensitivity reactions have occurred with NOVOLIN N. Inform patients on the symptoms of hypersensitivity reactions and to seek medical attention if they occur [see Warnings and Precautions (5.5)].

Novolin®, FlexPen® and Novo Nordisk® are registered trademarks of Novo Nordisk A/S.

ReliOn® is a registered trademark of Walmart Inc. and is used under license by Novo Nordisk Inc.

Patent Information: http://novonordisk-us.com/products/product-patents.html

© 2022 Novo Nordisk

Manufactured by:

Novo Nordisk Inc.

800 Scudders Mill Road

Plainsboro, NJ 08536

1-800-727-6500

U.S. License Number 1261

For information about NOVOLIN N contact:

Novo Nordisk Inc.

800 Scudders Mill Road

Plainsboro, NJ 08536

www.novonordisk-us.com

1-800-727-6500 (Se habla español)

Patient Package Insert

Patient Information

NOVOLIN® N (No-voe-lin)

(insulin isophane human) injectable suspension, for subcutaneous use

Do not share your Novolin N FlexPen or syringes with other people, even if the needle has been changed. You may give other people a serious infection or get a serious infection from them.

What is Novolin N?

Novolin N is a man-made insulin that is used to control high blood sugar in adults and children with diabetes mellitus.

Who should not use Novolin N?

Do not use Novolin N if you:

- are having an episode of low blood sugar (hypoglycemia).
- have an allergy to isophane insulin human or any of the ingredients in Novolin N. See the end of this Patient Information leaflet for a complete list of ingredients in Novolin N.

Before using Novolin N, tell your healthcare provider about all of your medical conditions, including if you:

- have liver or kidney problems.
- take any other medicines, especially ones called TZDs (thiazolidinediones).
- have heart failure or other heart problems. If you have heart failure, it may get worse while you take TZDs with Novolin N.
- are pregnant or plan to become pregnant. Talk with your healthcare provider about the best way to control your blood sugar if you plan to become pregnant or while you are pregnant.
- are breastfeeding or plan to breastfeed. Novolin N may pass into your breast milk. Talk with your healthcare provider about the best way to feed your baby while using Novolin N.

Tell your healthcare provider about all of the medicines you take, including prescription and over-the-counter medicines, vitamins and herbal supplements.

Before you start using Novolin N, talk to your healthcare provider about low blood sugar and how to manage it.

How should I use Novolin N?

- Read the detailed Instructions for Use that comes with your Novolin N.
- Use Novolin N exactly as your healthcare provider tells you to. Your healthcare provider should tell you how much Novolin N to use and when to use it.
- Know the type, strength, and amount of insulin you use. Do not change the type or amount of insulin you use unless your healthcare provider tells you to. The amount of insulin and the best time for you to take your insulin may need to change if you use different types of insulin.
- Check your insulin label each time you give your injection to make sure you are using the correct insulin.
- Inject Novolin N under the skin (subcutaneously) of your stomach area, buttocks, upper legs (thighs), or upper arms. Do not inject Novolin N into your vein (intravenously) or use in an insulin infusion pump.
- Do not mix Novolin N with any other insulin except NOVOLIN R. If Novolin N is mixed with NOVOLIN R, the NOVOLIN R should be drawn into the syringe first. Inject immediately after mixing.
- Change (rotate) your injection site within the area you choose with each dose to reduce your risk of getting lipodystrophy (pits in skin or thickened skin) and localized cutaneous amyloidosis (skin with lumps) at the injection sites.
- Do not use the exact same spot for each injection.
- Do not inject where the skin has pits, is thickened, or has lumps.
- Do not inject where the skin is tender, bruised, scaly or hard, or into scars or damaged skin.
- Check your blood sugar levels. Ask your healthcare provider what your blood sugars should be and when you should check your blood sugar levels.

Keep Novolin N and all medicines out of the reach of children.

Your dose of Novolin N may need to change because of:

● change in level of physical activity or exercise, weight gain or loss, increased stress, illness, change in diet,

or because of other medicines you take.

What should I avoid while using Novolin N?

While using Novolin N do not:

- drive or operate heavy machinery until you know how Novolin N affects you.
- drink alcohol or use prescription or over-the-counter medicines that contain alcohol.

What are the possible side effects of Novolin N?

Novolin N may cause serious side effects that can lead to death, including:

- low blood sugar (hypoglycemia). Signs and symptoms of low blood sugar may include:
  - dizziness or lightheadedness, sweating, confusion, headache, blurred vision, slurred speech, shakiness, fast heartbeat, anxiety, irritability or mood changes, hunger.
  - Your healthcare provider may prescribe a glucagon emergency kit so that others can give you an injection if your blood sugar becomes too low (hypoglycemia) and you are unable to take sugar by mouth.
- severe allergic reaction (whole body reaction). Get medical help right away if you have any of these signs or symptoms of a severe allergic reaction:
  - a rash over your whole body, have trouble breathing, a fast heartbeat, or sweating.
- low potassium in your blood (hypokalemia).
- heart failure. Taking certain diabetes pills called thiazolidinediones or “TZDs” with Novolin N may cause heart failure in some people. This can happen even if you have never had heart failure or heart problems before. If you already have heart failure it may get worse while you take TZDs with Novolin N. Your healthcare provider should monitor you closely while you are taking TZDs with Novolin N. Tell your healthcare provider if you have any new or worse symptoms of heart failure including:
- shortness of breath, swelling of your ankles or feet, sudden weight gain.

Treatment with TZDs and Novolin N may need to be adjusted or stopped by your healthcare provider if you have new or worse heart failure.

Get emergency medical help if you have:
2. severe hypoglycemia needing hospitalization or emergency room care, and be sure to tell the hospital staff the units of Novolin N your healthcare provider has prescribed for you.
3. trouble breathing, shortness of breath, fast heartbeat, swelling of your face, tongue, or throat, sweating, extreme drowsiness, dizziness, confusion.
The most common side effects of Novolin N include:
5. low blood sugar (hypoglycemia), allergic reactions including reactions at your injection site, skin thickening or pits at the injection site (lipodystrophy), weight gain, and swelling (edema) in hands or feet.

These are not all of the possible side effects of Novolin N. Call your doctor for medical advice about side effects. You may report side effects to FDA at 1-800-FDA-1088.

General information about the safe and effective use of Novolin N

Medicines are sometimes prescribed for purposes other than those listed in a Patient Information leaflet. Do not use Novolin N for a condition for which it was not prescribed. Do not give Novolin N to other people, even if they have the same symptoms you have. It may harm them.

This Patient Information leaflet summarizes the most important information about Novolin N. If you would like more information, talk with your healthcare provider. You can ask your healthcare provider or pharmacist for information about Novolin N that is written for healthcare providers.

For more information, call 1-800-727-6500 or visit www.novonordisk-us.com.

What are the ingredients in Novolin N?

Active ingredient: insulin isophane human

Inactive ingredients: dibasic sodium phosphate, glycerin, metacresol, phenol, protamine sulfate, zinc, Water for Injection. Hydrochloric acid and sodium hydroxide may be added.

Novolin®, FlexPen® and Novo Nordisk® are registered trademarks of Novo Nordisk A/S.

© 2022 Novo Nordisk

Manufactured by:

Novo Nordisk Inc.

800 Scudders Mill Road

Plainsboro, New Jersey 08536

U.S. License Number 1261

For information about Novolin N contact:

Novo Nordisk Inc.

800 Scudders Mill Road

Plainsboro, New Jersey 08536

1-800-727-6500 (Se habla español)

www.novonordisk-us.com

This Patient Information has been approved by the U.S. Food and Drug Administration.

Revised: 11/2022

INSTRUCTIONS FOR USE

Novolin® N

(insulin isophane human)

injectable suspension, for subcutaneous use

10 mL multiple-dose vial (100 units/mL (U-100))

Before starting, gather all of the supplies that you will need to use for preparing and giving your insulin injection.

Never re-use syringes and needles.

How should I use the Novolin N vial?

1. Check to make sure that you have the correct type of insulin. This is especially important if you use different types of insulin.
2. Look at the vial and the insulin. The insulin should be a cloudy or milky suspension. The tamper-resistant cap should be in place before the first use. If the cap had been removed before your first use of the vial, or if the precipitate (the white deposit at the bottom of the vial) has become lumpy or granular in appearance or has formed a deposit of solid particles on the wall of the vial, do not use it and call Novo Nordisk at 1-800-727-6500.
3. Wash your hands with soap and water. If you clean your injection site with an alcohol swab, let the injection site dry before you inject. Talk with your healthcare provider about how to rotate injection sites and how to give an injection.
4. If you are using a new vial, pull off the tamper-resistant cap. Wipe the rubber stopper with an alcohol swab.
5. Roll the vial gently 10 times in your hands to mix it. This procedure should be carried out with the vial in a horizontal position. The rolling procedure must be repeated until the suspension appears uniformly white and cloudy. Shaking right before the dose is drawn into the syringe may cause bubbles or froth, which could cause you to draw up the wrong dose of insulin.
6. Pull back the plunger on the syringe until the black tip reaches the marking for the number of units you will inject.
7. Push the needle through the rubber stopper of the vial, and push the plunger all the way in to force air into the vial.
8. Turn the vial and syringe upside down and slowly pull the plunger back to a few units beyond the correct dose.
9. If there are any air bubbles, tap the syringe gently with your finger to raise the air bubbles to the top. Then slowly push the plunger to the marking for your correct dose. This process should move any air bubbles present in the syringe back into the vial.
10. Check to make sure you have the right dose of Novolin N in the syringe.
11. Pull the syringe with needle out of the vial’s rubber stopper.
12. Novolin N can be injected under the skin (subcutaneously) of your stomach area, buttocks, upper legs (thighs), or upper arms. Change (rotate) your injection sites within the area you choose for each dose to reduce your risk of getting lipodystrophy (pits in skin or thickened skin) and localized cutaneous amyloidosis (skin with lumps) at the injection sites. For each injection, change (rotate) your injection site within the area of skin that you use. Do not use the same injection site for each injection. Do not inject where the skin has pits, is thickened, or has lumps. Do not inject where the skin is tender, bruised, scaly or hard, or into scars or damaged skin. Your doctor should tell you if you need to pinch the skin before inserting the needle. This can vary from patient to patient, so it is important to ask your doctor if you did not receive instructions on pinching the skin. Insert the needle into the skin. Press the plunger of the syringe to inject the insulin. When you are finished injecting the insulin, pull the needle out of your skin. You may see a drop of Novolin N at the needle tip. This is normal and has no effect on the dose you just received. If you see blood after you take the needle out of your skin, press the injection site lightly with a piece of gauze or an alcohol wipe. Do not rub the area.
13. After your injection, do not recap the needle. Place used syringes, needles and used insulin vials in a disposable puncture-resistant sharps container, or some type of hard plastic or metal container with a screw on cap such as a detergent bottle or coffee can.
14. Ask your healthcare provider about the right way to throw away used syringes and needles. There may be state or local laws about the right way to throw away used syringes and needles. Do not throw away used needles and syringes in household trash or recycle.

How should I mix Novolin N with Novolin R?

Different insulins should be mixed only under instruction from a healthcare provider. Do not mix Novolin N with any other type of insulin besides Novolin R. Novolin N should be mixed only when injections with syringes are used. Insulin syringes may vary in the amount of space between the bottom line and the needle (“dead space”), so if you are mixing two types of insulin be sure to discuss any change in the model and brand of syringe you are using with your healthcare provider. Novolin N can be mixed with Novolin R right before use. When you are mixing Novolin N insulin with Novolin R, always draw the Novolin R (clear) into the syringe first.

1. Add together the doses (total number of units) of Novolin R and Novolin N that you need to inject. The total dose will determine the final amount (volume) in the syringe after drawing up both insulins into the syringe. For example, if you need 5 units of Novolin N and 2 units of Novolin R, the total dose of insulin in the syringe would be 7 units.
2. Roll the Novolin N vial between your hands until the liquid is equally cloudy throughout.
3. Draw into the syringe the same amount of air as the Novolin N dose. Inject this air into the Novolin N vial and then remove the needle from the vial but do not withdraw any of the Novolin N insulin. (Transferring Novolin N to the Novolin R vial will contaminate the Novolin R vial and may change how quickly it works.)
4. Draw into the syringe the same amount of air as the Novolin R dose. Inject this air into the Novolin R vial. With the needle in place, turn the vial upside down and withdraw the correct dose of Novolin R. The tip of the needle must be in the Novolin R to get the full dose and not an air dose.
5. After withdrawing the needle from the Novolin R vial, insert the needle into the Novolin N vial. Turn the Novolin N vial upside down with the syringe and needle still in it. Withdraw the correct dose of Novolin N.
6. Inject right away to avoid changes in how quickly the insulin works.

How should I store Novolin® N?

- Do not freeze Novolin N. Do not use Novolin N if it has been frozen.
- Keep Novolin N away from heat or light.
- All unopened vials:
  - Store unopened Novolin N vials in the refrigerator at 36°F to 46°F (2°C to 8°C).
  - Unopened vials may be used until the expiration date printed on the label, if they have been stored in the refrigerator.
  - Unopened vials should be thrown away after 42 days, if they are stored at room temperature up to 77°F (25°C).
- After vials have been opened:
- Opened Novolin N vials can be stored at room temperature up to 77°F (25°C). Do not refrigerate.
- Throw away all opened Novolin N vials after 42 days, even if they still have insulin left in them.

This Patient Instructions for Use has been approved by the Food and Drug Administration.

Manufactured by:

Novo Nordisk Inc.

800 Scudders Mill Road

Plainsboro, NJ 08536

1-800-727-6500

U.S. License Number 1261

Revised: 11/2022

INSTRUCTIONS FOR USE

Novolin® N FlexPen®

(insulin isophane human)

injectable suspension, for subcutaneous use

Introduction

Please read the following instructions carefully before using your Novolin N FlexPen.

Do not share your Novolin N FlexPen with other people, even if the needle has been changed. You may give other people a serious infection, or get a serious infection from them.

Novolin N FlexPen is a disposable, single-patient-use, dial-a-dose insulin pen. You can select doses from 1 to 60 units in increments of 1 unit. Novolin N FlexPen is designed to be used with NovoFine, NovoFine Plus or NovoTwist needles.

People who are blind or have vision problems should not use Novolin N FlexPen without help from a person trained to use Novolin N FlexPen.

Getting ready

Make sure you have the following items:

- Novolin N FlexPen
- New NovoFine, NovoFine Plus or NovoTwist needle
- Alcohol swab
- Gauze pad

Preparing your Novolin N FlexPen

Wash your hands with soap and water. Before you start to prepare your injection, check the label to make sure that you are taking the right type of insulin. This is especially important if you take more than 1 type of insulin. Novolin N should look white and cloudy after mixing.

A. Let the insulin reach room temperature before you use it. This makes it easier to mix.

Pull off the pen cap (see diagram A).

B. Gently move the pen up and down twenty times between position 1 and 2 as shown, so the glass ball moves from one end of the cartridge to the other (see diagram B).

Repeat moving the pen until the liquid appears white and cloudy. Do not use the pen if the liquid appears discolored or contains particles.

For every following injection move the pen up and down between positions 1 and 2 at least ten times until the liquid appears white and cloudy.

After mixing, complete all the following steps of the injection right away. If there is a delay, the insulin will need to be mixed again.

Before you inject, there must be at least 12 units of insulin left in the cartridge to make sure the remaining insulin is

evenly mixed. If there are less than 12 units left in your Novolin N FlexPen, use a new pen.

Wipe the rubber stopper with an alcohol swab.

Attaching the needle

C. Remove the protective tab from a disposable needle.

Screw the needle tightly onto your Novolin N FlexPen. It is important that the needle is put on straight (see diagram C).

Never place a disposable needle on your Novolin N FlexPen until you are ready to take your injection.

D. Pull off the big outer needle cap (see diagram D).

E. Pull off the inner needle cap and dispose of it (see diagram E).

Always use a new needle for each injection to help ensure sterility and prevent blocked needles. Do not reuse or share

your needles with other people. You may give other people a serious infection, or get a serious infection from them.

Be careful not to bend or damage the needle before use.

To reduce the risk of unexpected needle sticks, never put the inner needle cap back on the needle.

Giving the airshot before each injection

Before each injection small amounts of air may collect in the cartridge during normal use. To avoid injecting air and to make sure you take the right dose of insulin:

F. Turn the dose selector to select 2 units (see diagram F).

G. Hold your Novolin N FlexPen with the needle pointing up. Tap the cartridge gently with your finger a few times to make any air bubbles collect at the top of the cartridge (see diagram G).

H. Keep the needle pointing upwards, press the push-button all the way in (see diagram H). The dose selector returns to 0.

A drop of insulin should appear at the needle tip. If not, change the needle and repeat the procedure no more than 6 times.

If you do not see a drop of insulin after 6 times, do not use the Novolin N FlexPen and contact Novo Nordisk at 1-800-727-6500.

A small air bubble may remain at the needle tip, but it will not be injected.

Selecting your dose

Check and make sure that the dose selector is set at 0.

I. Turn the dose selector to the number of units you need to inject. The pointer should line up with your dose.

The dose can be corrected either up or down by turning the dose selector in either direction until the correct dose lines up with the pointer (see diagram I). When turning the dose selector, be careful not to press the push-button as insulin will come out.

You cannot select a dose larger than the number of units left in the cartridge.

You will hear a click for every single unit dialed. Do not set the dose by counting the number of clicks you hear.

Do not use the cartridge scale printed on the cartridge to measure your dose of insulin.

Giving the injection

Give the injection exactly as shown to you by your healthcare provider. Your healthcare provider should tell you if you need to pinch the skin before injecting. Wipe the skin with an alcohol swab and let the area dry.

Novolin N can be injected under the skin (subcutaneously) of your stomach area, buttocks, upper legs (thighs), or upper arms.

Change (rotate) your injection sites within the area you choose for each dose to reduce your risk of getting lipodystrophy (pits in skin or thickened skin) and localized cutaneous amyloidosis (skin with lumps) at the injection sites. Do not use the same injection site for each injection. Do not inject where the skin has pits, is thickened, or has lumps. Do not inject where the skin is tender, bruised, scaly or hard, or into scars or damaged skin.

J. Insert the needle into your skin.

Inject the dose by pressing the push-button all the way in until the 0 lines up with the pointer (see diagram J). Be careful only to push the button when injecting.

Turning the dose selector will not inject insulin.

K. Keep the needle in the skin for at least 6 seconds, and keep the push-button pressed all the way in until the needle has been pulled out from the skin (see diagram K). This will make sure that the full dose has been given.

You may see a drop of insulin at the needle tip. This is normal and has no effect on the dose you just received. If blood appears after you take the needle out of your skin, press the injection site lightly with a gauze pad or an alcohol swab. Do not rub the area.

After the injection

Do not recap the needle. Recapping can lead to a needle stick injury. Remove the needle from the Novolin N FlexPen after each injection and dispose of it. This helps to prevent infection, leakage of insulin, and will help to make sure you inject the right dose of insulin.

If you do not have a sharps container, carefully slip the needle into the outer needle cap. Safely remove the needle and throw it away as soon as you can.

- The used Novolin N FlexPen may be thrown away in your household trash after you have removed the needle.
- Put your used needles in a FDA-cleared sharps disposal container right away after use. Do not throw away (dispose of) loose needles in your household trash.
- If you do not have a FDA-cleared sharps disposal container, you may use a household container that is:
- made of a heavy-duty plastic
- can be closed with a tight-fitting, puncture-resistant lid, without sharps being able to come out
- upright and stable during use
- leak-resistant
- properly labeled to warn of hazardous waste inside the container
- When your sharps disposal container is almost full, you will need to follow your community guidelines for the right way to dispose of your sharps disposal container. There may be state or local laws about how you should throw away used needles and syringes. For more information about safe sharps disposal, and for specific information about sharps disposal in the state that you live in, go to the FDA’s website at: http://www.fda.gov/safesharpsdisposal.
Do not dispose of your used sharps disposal container in your household trash unless your community guidelines permit this. Do not recycle your used sharps disposal container.
- When there is not enough medicine left in your Novolin N FlexPen for your prescribed dose, the Novolin N FlexPen may be thrown away in your household trash after you have removed the needle. The Novolin N FlexPen prevents the cartridge from being completely emptied. It is designed to deliver 300 units.

L. Put the pen cap on the Novolin N FlexPen and store the Novolin N FlexPen without the needle attached (see diagram L). Storing without the needle attached helps prevent leaking, blocking of the needle, and air from entering the Pen.

How should I store Novolin N FlexPen?
      - Do not freeze Novolin N. Do not use Novolin N if it has been frozen.
      - Keep Novolin N away from heat and light.
      - Until first use:
5. Store unused Novolin N FlexPen in the refrigerator at 36°F to 46°F (2°C to 8°C).
6. Unused Novolin N FlexPen may be used until the expiration date printed on the label, if kept in the refrigerator at 36°F to 46°F (2°C to 8°C).
7. Unused Novolin N FlexPen stored at room temperature should be thrown away after 28 days.
      - In-use:
9. Store the Novolin N FlexPen you are currently using out of the refrigerator at room temperature up to 86°F (30°C) for up to 28 days.
10. The Novolin N FlexPen you are using should be thrown away after 28 days, even if it still has insulin left in it.
11. Store the Novolin N FlexPen without the needle attached.

Maintenance

For the safe and proper use of your Novolin N FlexPen be sure to handle it with care. Avoid dropping your Novolin N FlexPen as it may damage it. If you are concerned that your Novolin N FlexPen is damaged, use a new one. You can clean the outside of your Novolin N FlexPen by wiping it with a damp cloth. Do not soak or wash your Novolin N FlexPen as it may damage it. Do not refill your Novolin N FlexPen.

Remove the needle from Novolin N FlexPen after each injection. This helps to ensure sterility, prevent leakage of

insulin, and will help to make sure you inject the right dose of insulin for future injections.

Be careful when handling used needles to avoid needle sticks and transfer of infectious diseases.

Keep your Novolin N FlexPen and needles out of the reach of children.

Use Novolin N FlexPen as directed to treat your diabetes.

Do not share your Novolin N FlexPen or needles with other people. You may give other people a serious infection,

or get a serious infection from them.

Always use a new needle for each injection.

Novo Nordisk is not responsible for harm due to using this insulin pen with products not recommended by Novo

Nordisk.

As a precautionary measure, always carry a spare insulin delivery device in case your Novolin N FlexPen is lost or

damaged.

Remember to keep the disposable Novolin N FlexPen with you. Do not leave it in a car or other location where it can

get too hot or too cold.

This Instructions for Use has been approved by the U.S. Food and Drug Administration.

Manufactured by:

Novo Nordisk Inc.

800 Scudders Mill Road

Plainsboro, NJ 08536

1-800-727-6500

U.S. License Number 1261

Revised: 11/2022